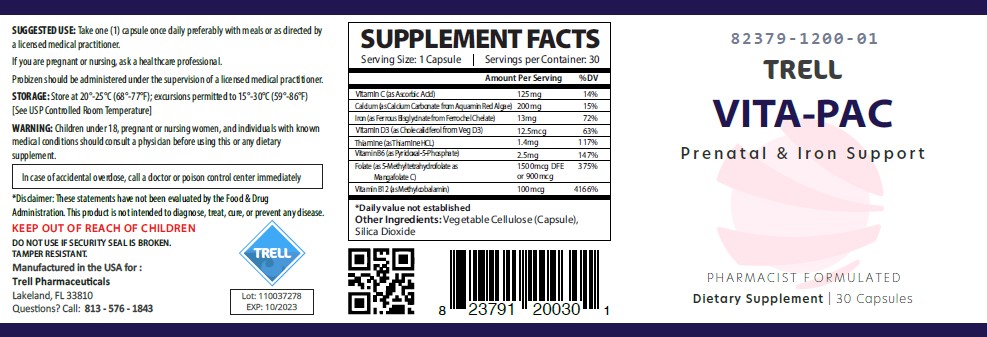 DRUG LABEL: Vita-Pac
NDC: 82379-1200 | Form: CAPSULE
Manufacturer: Trell Pharma
Category: other | Type: DIETARY SUPPLEMENT
Date: 20230326

ACTIVE INGREDIENTS: ASCORBIC ACID 125 mg/1 1; cholecalciferol 0.0125 mg/1 1; THIAMINE HYDROCHLORIDE 1.4 mg/1 1; PYRIDOXAL PHOSPHATE ANHYDROUS 2.5 mg/1 1; FOLATE SODIUM 0.9 mg/1 1; METHYLCOBALAMIN 0.1 mg/1 1; CALCIUM CARBONATE 200 mg/1 1; IRON 13 mg/1 1
INACTIVE INGREDIENTS: SILICON DIOXIDE

Vita-Pac (Prenatal & Iron Supplement)

HEALTH CLAIM:

Vita-Pac Capsule - Prenatal/Postnatal/Folate Health Dietary Supplement

Supplement Facts
Serving Size: 1 Capsule
Servings per Bottle: 30
Amount Per Serving: | % Daily Value
Vitamin C (as Ascorbic Acid) | 125 mg | 104%
Calcium (as Calcium Carbonate from Aquamin Red Algae) | 200 mg | 15%
Iron (as Ferrous Bisglycinate from Ferrochel Chelate) | 13 mg | 72%
Vitamin D3 (as Cholecaliciferol from Veg D3) | 12.5 mcg | 63%
Thiamine (as Thiamine HCL) | 1.4 mg | 117%
Vitamin B6 (as Pyridoxal-5-Phosphate) | 2.5 mg | 147%
Folate (as 5-Methyltetrahydrofolate as Mangafolate-C) | 900 mcg | 375%
Vitamin B12 (as Methylcobalamin) | 100 mcg | 4,166%

OTHER INGREDIENTS: Vegetable Cellulose (Capsule), Silica Dioxide

WARNING AND PRECAUTIONS

This product is contraindicated in patients with a known hypersensitivity to any of the ingredients.

Vita-Pac should only be used under the direction and supervision of a licensed medical practitioner.

WARNING: Children under 18, pregnant or nursing women, and individuals with known medical conditions should consult a physician before using this or any dietary supplement.

In case of accidental overdoes, call a doctor or poison control center immediately.

KEEP OUT OF REACH OF CHILDREN

STORAGE

Store at 20°-25°C (68°-77°F); excursions permitted to 15°-30°C (59°-86°F).

DOSAGE & ADMINISTRATION

Take one (1) capsule once daily preferably with meals or as directed by medical practitioner.

If you are pregnant or nursing, ask a healthcare professional.

Vita-Pac should be administered under the supervision of a licensed medical practitioner.

HOW SUPPLIED HEALTH CLAIM:

Vita-Pac

Dietary Supplement

NHRIC: 82379-1200-01 *

Bottles contain 30 Capsules

Distributed in the USA by:
Trell Pharma, LLC

† The most appropriate way to ensure pedigree reporting consistent with these regulatory guidelines and safety monitoring is to dispense this product by prescription. This is not an Orange Book product.

*Trell Pharma does not represent these product codes to be National Drug Codes (NDC). Product codes are formatted according to standard industry practice, to meet the formatting requirement by pedigree reporting and supply-chain control including pharmacies.

1. Federal Register Notice of August 2, 1973 (38 FR 20750)
2. Federal Register Notice of October 17, 1980 (45 FR 69043, 69044)
3. Federal Register Notice of March 5, 1996 (61 FR 8760)